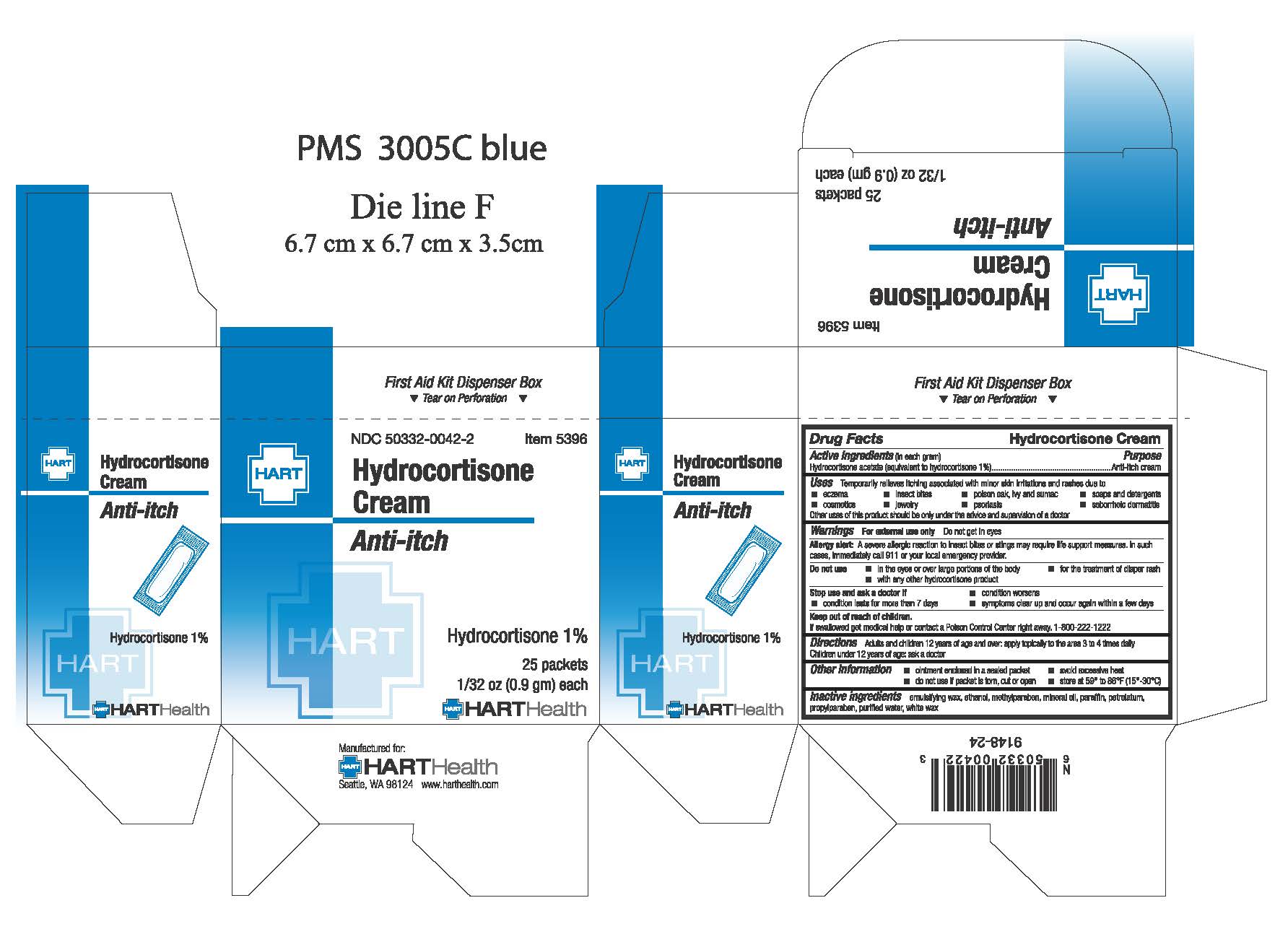 DRUG LABEL: HYDROCORTISONE
NDC: 50332-0042 | Form: CREAM
Manufacturer: HART Health
Category: otc | Type: HUMAN OTC DRUG LABEL
Date: 20240216

ACTIVE INGREDIENTS: HYDROCORTISONE ACETATE 10 mg/1 g
INACTIVE INGREDIENTS: ALCOHOL; METHYLPARABEN; MINERAL OIL; PARAFFIN; PROPYLPARABEN; WATER; WHITE WAX

HYDROCORTISONE CREAM

Active Ingredient (in each gram): Hydrocortisone Acetate 10mg (equivalent to Hydrocortisone 1%)

Purpose: anti-itch cream

WARNINGS

Warnings: For external use only. Do not get in eyes

Allergy alert: A severe allergic reaction to insect bites or stings may require life support measures. In such cases, immediately clal 911 or your local emergency provider.

Do not use:

- in the eyes or over large portions of the body
- for the treatment of diaper rash
- with any other hydrocortisone product

Stop use and ask a doctor if:

- condition worsens
- condition lasts for more than 7 days
- symptoms clear up and occur again within a few days

Keep out of reach of children. If swallowed get medical help or contact a Poison Control Center right away. 1-800-222-1222

Directions:

Adults and children 12 years of age and over: apply topically to the area 3 to 4 times daily.

Children under 12 years of age: do not use, ask a doctor

INACTIVE INGREDIENT

Inactive Ingredients: emulsifying wax, ethanol, methylparaben, mineral oil, paraffin, petrolatum, propylparaben, purified water, white wax